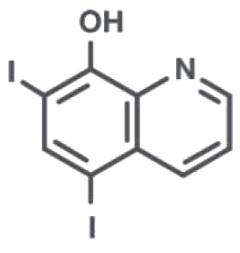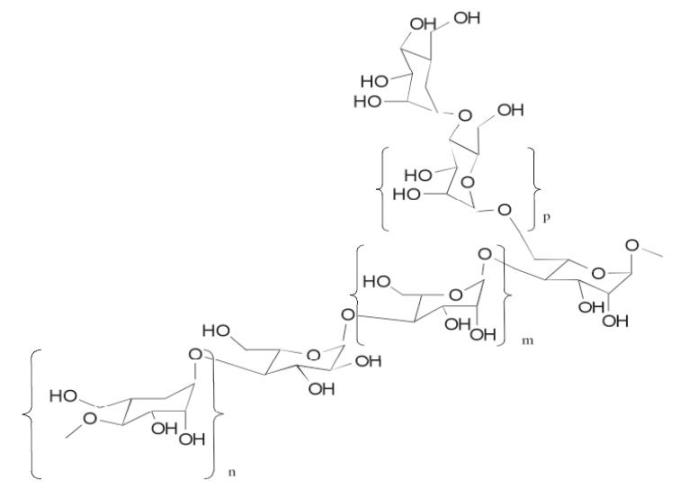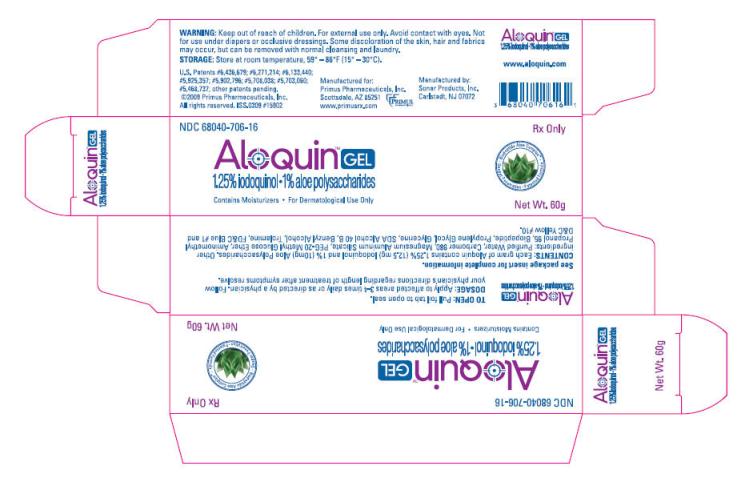 DRUG LABEL: Aloquin
NDC: 68040-706 | Form: GEL
Manufacturer: Primus Pharmaceuticals
Category: prescription | Type: HUMAN PRESCRIPTION DRUG LABEL
Date: 20091007

ACTIVE INGREDIENTS: Aloe Vera Leaf 10 mg/1 g; Iodoquinol 12.5 mg/1 g

ALOQUIN® gel
(1.25% Iodoquinol and 1% Aloe Polysaccharides)

Prescribing Information

DESCRIPTION

Each gram of ALOQUIN contains 1.25% (12.5 mg) Iodoquinol and 1% (10mg) Aloe Polysaccharides. Other ingredients: Purified Water, Carbomer 980, Magnesium Aluminum Silicate, PEG-20 Methyl Glucose Ether, Aminomethyl Propanol 95, Biopeptide, Propylene Glycol, Glycerine, SDA Alcohol 40 B, Benzyl Alcohol, Trolamine, FD&C Blue #1 and D&C Yellow #10.

Iodoquinol

Iodoquinol is an antifungal and antibacterial agent. Chemically, Iodoquinol is [5,7-diiodo-8-quinolinol] with the molecular formula (C9H5I2NO) and is represented by the following structural formula:

Aloe Polysaccharide

The Aloe Polysaccharide in ALOQUIN is a patented mixture of acetylated mannan aloe polysaccharide. Each purified acetylated mannan polysaccharide of specific molecular weight range and average is composed of the same repeating subunits shown below (where m is mannose, n is galactose and p is glucose monomers):

INDICATIONS AND USAGE

Based on a review of a related drug by the National Research Council and subsequent FDA classification for that drug, the indications are as follows: "Possibly" Effective: Contact or atopic dermatitis; impetiginized eczema; nummular eczema; endogenous chronic infectious dermatitis; stasis dermatitis; pyoderma; nuchal eczema and chronic eczematoid otitis externa; acne urticata; localized or disseminated neurodermatitis; lichen simplex chronicus; anogenital pruritus (vulvae, scroti, ani); folliculitis; bacterial dermatoses; mycotic dermatoses such as tinea (capitis, cruris, corporis, pedis); monliasis; intertrigo. Final classification of the less-than-effective indications requires further investigation.

CONTRAINDICATIONS

ALOQUIN is contraindicated in those patients with a history of hypersensitivity to any components of the preparation.

WARNINGS AND PRECAUTIONS

For external use only. Keep away from eyes. If irritation develops, the use of ALOQUIN should be discontinued and appropriate therapy instituted. Some discoloration of the skin, hair and fabrics may occur, but can be removed with normal cleansing and laundry. Not intended for use on infants or under diapers or occlusive dressings.

Iodoquinol may be absorbed through the skin and interfere with thyroid function tests. If such tests are contemplated, wait at least one month after discontinuance of therapy to perform these tests. The ferric chloride test for phenylketonuria (PKU) can yield a false positive result if Iodoquinol is present in the diaper or urine. Prolonged use may result in overgrowth of non-susceptible organisms requiring appropriate therapy. Keep out of reach of children.

Carcinogenesis, Mutagenisis and Impairment of Fertility

Long term animal studies have not been performed to evaluate the carcinogenic potential of the effect on fertility of Iodoquinol. Mutagenicity studies have not been performed with Iodoquinol.

Pregnancy Category C

TERATOGENIC EFFECTS

Animal reproductive studies have not been conducted with ALOQUIN. It is not known whether ALOQUIN can cause fetal harm when administered to pregnant women or can affect reproductive capacity. ALOQUIN should be given to pregnant women only if clearly needed.

Nursing Mothers

It is not known whether this drug is excreted in human milk. Because many drugs are excreted in human milk, caution should be exercised when ALOQUIN is administered to a nursing woman.

Pediatric Use

Safety and effectiveness in pediatric patients under the age of 12 have not been established.

ADVERSE REACTIONS

Adverse reactions from topical use of ALOQUIN is expected to be low when used as directed, due to low concentration of Iodoquinol present in this topical gel.

To achieve the equivalent of a common daily oral dose of nearly 2,000 mg Iodoquinol, one will need to use more than 2 full tubes of 60 g ALOQUIN in a single application. Adverse reactions from oral form of Iodoquinol (nearly 2,000 mg daily) have been reported: various forms of skin eruptions, hives, itching, nausea, vomiting, abdominal cramps, diarrhea, anusitis, fever, chills, headache, vertigo and enlargement of thyroid.

DOSAGE AND ADMINISTRATION

Apply to affected areas 3-4 times daily or as directed by a physician. Follow your physician's directions regarding length of treatment after symptoms resolve.

HOW SUPPLIED

NDC # 68040-706-16 | 60 gram gel tube
NDC # 68040-706-01 | 1 gram gel individual pack
NDC # 68040-706-08 | 10-count carton of 1 gram gel sample packs - not for resale

Each 1 gram gel pack contains multiple doses depending on the surface area treated.

STORAGE

Store at room temperature 15°-30°C (59°-86°F). Keep tightly closed.

Rx ONLY
www.aloquin.com

Manufactured for:
Primus Pharmaceuticals, Inc.
Scottsdale, AZ 85251
www.primusrx.com

Manufactured by:
Sonar Products, Inc.
Carlstadt, NJ 07072

U.S. Patents #6,436,679; #6,271,214; #6,133,440; #5,925,357; #5,902,796; #5,708,038; #5,703,060; #5,468,737; other patents pending.
©2009 Primus Pharmaceuticals, Inc. All rights reserved.

ISS.0309 #15905

PRINCIPAL DISPLAY PANEL - 60g Carton

NDC 68040-706-16

AloQuin™ GEL

1.25% iodoquinol • 1% aloe polysaccharides

Contains Moisturizers • For Dermatological Use Only

Rx Only

Biopeptide Aloe Complex™
Deeper Penetration • Patented Formula

Net Wt. 60g